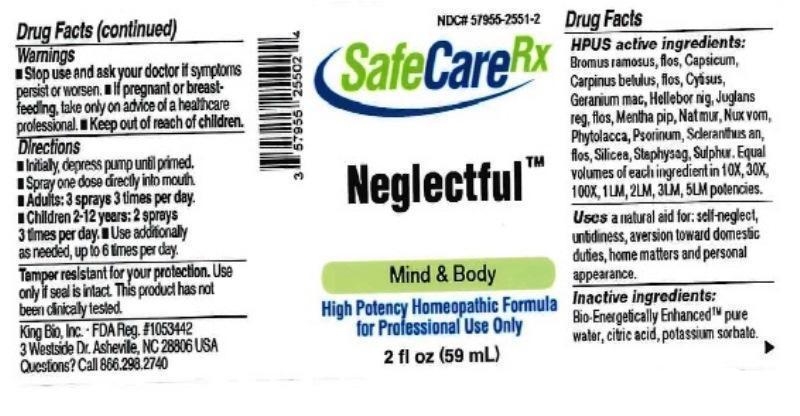 DRUG LABEL: Neglectful
NDC: 57955-2551 | Form: LIQUID
Manufacturer: King Bio Inc.
Category: homeopathic | Type: HUMAN OTC DRUG LABEL
Date: 20161209

ACTIVE INGREDIENTS: BROMUS RAMOSUS FLOWER 10 [hp_X]/59 mL; CAPSICUM 10 [hp_X]/59 mL; CARPINUS BETULUS FLOWERING TOP 10 [hp_X]/59 mL; CYTISUS SCOPARIUS FLOWERING TOP 10 [hp_X]/59 mL; GERANIUM MACULATUM ROOT 10 [hp_X]/59 mL; HELLEBORUS NIGER ROOT 10 [hp_X]/59 mL; JUGLANS REGIA FLOWERING TOP 10 [hp_X]/59 mL; MENTHA PIPERITA 10 [hp_X]/59 mL; SODIUM CHLORIDE 10 [hp_X]/59 mL; STRYCHNOS NUX-VOMICA SEED 10 [hp_X]/59 mL; PHYTOLACCA AMERICANA ROOT 10 [hp_X]/59 mL; SCABIES LESION LYSATE (HUMAN) 10 [hp_X]/59 mL; SCLERANTHUS ANNUUS FLOWERING TOP 10 [hp_X]/59 mL; SILICON DIOXIDE 10 [hp_X]/59 mL; DELPHINIUM STAPHISAGRIA SEED 10 [hp_X]/59 mL; SULFUR 10 [hp_X]/59 mL
INACTIVE INGREDIENTS: WATER; ANHYDROUS CITRIC ACID; POTASSIUM SORBATE

Neglectful™

ACTIVE INGREDIENT

Drug Facts_________________________________________________________________________________________________________

HPUS active ingredients: Bromus ramosus, flos, Capsicum annuum, Carpinus betulus, flos, Cytisus scoparius, Geranium maculatum, Helleborus niger, Juglans regia, flos, Mentha piperita, Natrum muriaticum, Nux vomica, Phytolacca decandra, Psorinum, Scleranthus annuus, flos, Silicea, Staphysagria, Sulphur. Equal volumes of each ingredient in 10X, 30X, 100X, 1LM, 2LM, 3LM, 5LM potencies.

INDICATIONS AND USAGE

Uses a natural aid for: self-neglect, untidiness, aversion toward domestic duties, home matters and personal appearance.

Inactive Ingredients:

Bio-Energetically Enhanced™ pure water, citric acid and potassium sorbate.

Warnings

- Stop use and ask your doctor if symptoms persist or worsen.
- If pregnant or breast-feeding, take only on advice of a healthcare professional.

- Keep out of reach of children.

Directions

- Initially, depress pump until primed.
- Spray one dose directly into mouth.
- Adults: 3 sprays 3 times per day.
- Children 2-12: 2 sprays 3 times per day.
- Use additionally as needed, up to 6 times per day.

OTHER SAFETY INFORMATION

Tamper resistant for your protection. Use only if safety seal is intact. This product has not been clinically tested.

PURPOSE

Uses a natural aid for:

- self-neglect
- untidiness
- aversion toward domestic duties
- home matters
- personal appearance